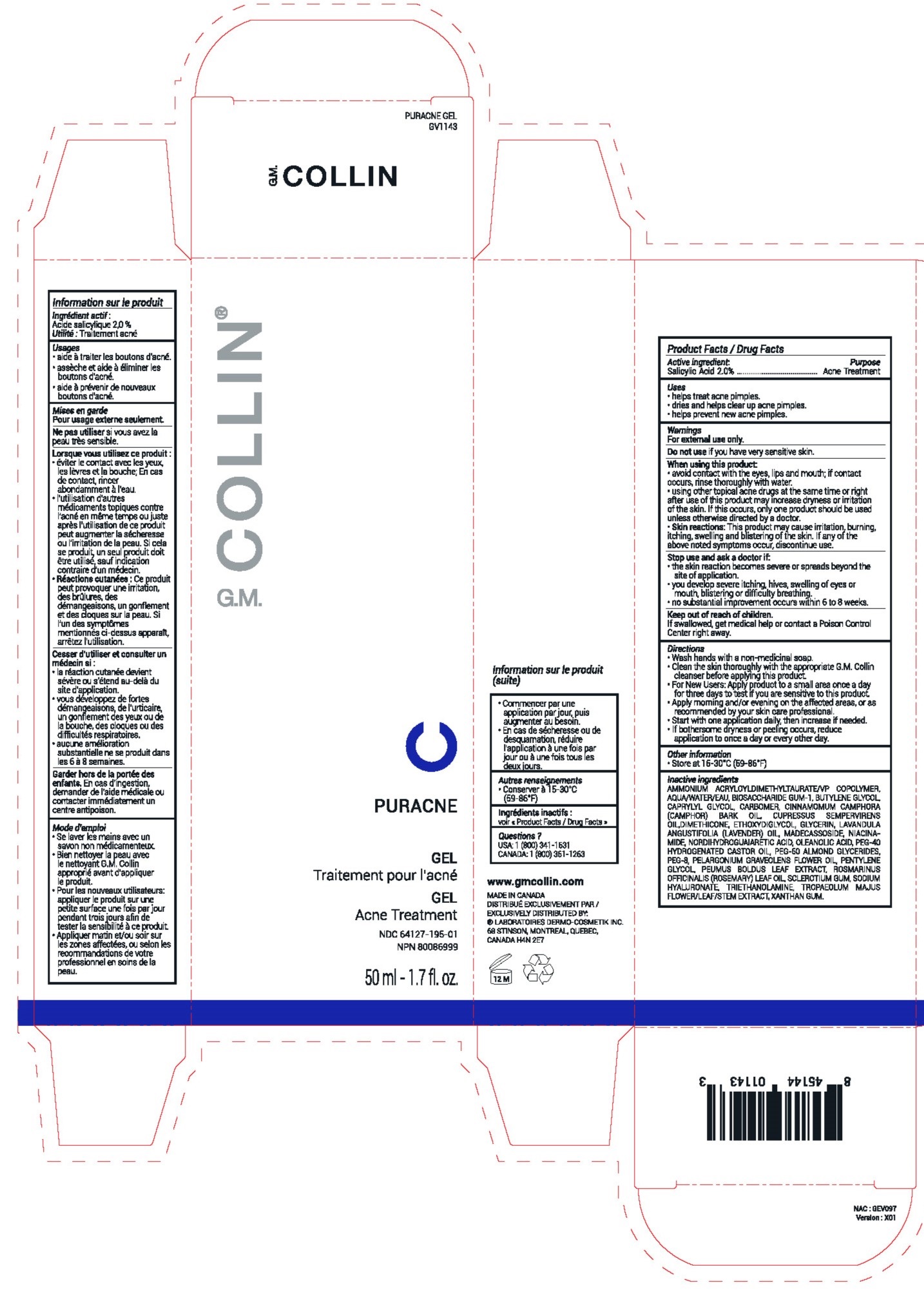 DRUG LABEL: GM COLLIN PURACNE
NDC: 64127-195 | Form: GEL
Manufacturer: Laboratoires Dermo-Cosmetik Inc.
Category: otc | Type: HUMAN OTC DRUG LABEL
Date: 20251209

ACTIVE INGREDIENTS: SALICYLIC ACID 20 mg/1 mL
INACTIVE INGREDIENTS: AMMONIUM ACRYLOYLDIMETHYLTAURATE/VP COPOLYMER; BIOSACCHARIDE GUM-1; BUTYLENE GLYCOL; CAPRYLYL GLYCOL; CARBOMER HOMOPOLYMER, UNSPECIFIED TYPE; CAMPHOR OIL; DIMETHICONE; DIETHYLENE GLYCOL MONOETHYL ETHER; GLYCERIN; MADECASSOSIDE; NIACINAMIDE; OLEANOLIC ACID; POLYETHYLENE GLYCOL 400; POLYOXYL 40 HYDROGENATED CASTOR OIL; PEG-60 ALMOND GLYCERIDES; PELARGONIUM GRAVEOLENS FLOWER OIL; PENTYLENE GLYCOL; BETASIZOFIRAN; HYALURONATE SODIUM; TROLAMINE; XANTHAN GUM; WATER; PHENOXYETHANOL; BIOTIN; ETHYLHEXYLGLYCERIN; SODIUM METABISULFITE; PEUMUS BOLDUS LEAF; TROPAEOLUM MAJUS FLOWERING TOP; ROSEMARY OIL; MASOPROCOL; SODIUM CITRATE; CITRIC ACID MONOHYDRATE; LAVENDER OIL; CUPRESSUS SEMPERVIRENS LEAF OIL

G.M. COLLIN®PURACNE GEL

Product / Drug Facts

Active ingredient

Salicylic Acid 2.0%

Purpose

Acne Treatment

Uses

- Helps treat acne pimples.
- Dries and helps clear up acne pimples.
- Helps prevent new acne pimples.

Warnings

For external use only.

Do not useif you have very sensitive skin.

When using this product

- Avoid contact with the eyes, lips and mouth; if contact occurs, rinse thoroughly with water.
- Using other topical acne drugs at the same time or right after use of this product may increase dryness or irritation of the skin. If this occurs, only one product should be used unless otherwise directed by a doctor.
- Skin reactions:This product may cause irritation, burning, itching, swelling and blistering of the skin. If any of the above noted symptoms occur, discontinue use.

Stop use and ask a doctor if

- The skin reaction becomes severe or spreads beyond the site of application.
- You develop severe itching, hives, swelling of eyes or mouth, blistering or difficulty breathing.
- No substantial improvement occurs within 6 to 8 weeks.

Keep out of reach of children.If swallowed, get medical help or contact a Poison Control Center right away.

Directions

- Wash hands with a non-medicinal soap.
- Clean the skin thoroughly with the appropriate G.M. Collin cleanser before applying this product.
- For New Users: Apply product to a small area once a day for three days to test if you are sensitive to this product.
- Apply morning and/or evening on the affected areas, or as recommended by your skin care professional.
- Start with one application daily, then increase if needed.
- If bothersome dryness or peeling occurs, reduce application to once a day or every other day.

Other information

Store at 15-30°C (59-86°F).

Inactive ingredients

AMMONIUM ACRYLOYLDIMETHYLTAURATE/VP COPOLYMER, AQUA/WATER/EAU, BIOSACCHARIDE GUM-1, BUTYLENE GLYCOL, CAPRYLYL GLYCOL, CARBOMER, CINNAMOMUM CAMPHORA (CAMPHOR) BARK OIL, CUPRESSUS SEMPERVIRENS OIL,DIMETHICONE, ETHOXYDIGLYCOL, GLYCERIN, LAVANDULA ANGUSTIFOLIA (LAVENDER) OIL, MADECASSOSIDE, NIACINAMIDE, NORDIHYDROGUAIARETIC ACID, OLEANOLIC ACID, PEG-40 HYDROGENATED CASTOR OIL, PEG-60 ALMOND GLYCERIDES, PEG-8, PELARGONIUM GRAVEOLENS FLOWER OIL, PENTYLENE GLYCOL, PEUMUS BOLDUS LEAF EXTRACT, ROSMARINUS OFFICINALIS (ROSEMARY) LEAF OIL, SCLEROTIUM GUM, SODIUM HYALURONATE, TRIETHANOLAMINE, TROPAEOLUM MAJUS FLOWER/LEAF/STEM EXTRACT, XANTHAN GUM.

Questions?

USA: 1 (800) 341-1531 /
CANADA: 1 (800) 361-1263

www.gmcollin.com
MADE IN CANADA
DISTRIBUÉ EXCLUSIVEMENT PAR /
EXCLUSIVELY DISTRIBUTED BY:
® LABORATOIRES DERMO-COSMETIK INC.
68 STINSON, MONTREAL, QUEBEC,
CANADA H4N 2E7

PRINCIPAL DISPLAY PANEL - 50 ml Tube Carton

G.M. COLLIN

PURACNE
GEL

Acne Treatment

NDC 64127-195-01
NPN 80086999

50 ml - 1.7 fl. oz

.